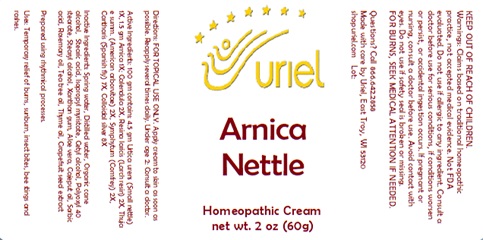 DRUG LABEL: Arnica Nettle
NDC: 48951-1385 | Form: CREAM
Manufacturer: Uriel Pharmacy Inc.
Category: homeopathic | Type: HUMAN OTC DRUG LABEL
Date: 20241216

ACTIVE INGREDIENTS: ARNICA MONTANA FLOWER 1 [hp_X]/1 g; LARIX DECIDUA RESIN 2 [hp_X]/1 g; THUJA OCCIDENTALIS WHOLE 2 [hp_X]/1 g; URTICA URENS 1 [hp_X]/1 g; LYTTA VESICATORIA 7 [hp_X]/1 g; CALENDULA OFFICINALIS FLOWERING TOP 2 [hp_X]/1 g; COMFREY ROOT 2 [hp_X]/1 g; SILVER 8 [hp_X]/1 g
INACTIVE INGREDIENTS: WATER; STEARIC ACID; ALOE VERA LEAF; CAJUPUT OIL; ROSEMARY OIL; THYME OIL; SORBIC ACID; TEA TREE OIL; CITRUS PARADISI SEED; ALCOHOL; ISOPROPYL MYRISTATE; CETYL ALCOHOL; POLYOXYL 40 STEARATE; STEARYL ALCOHOL; XANTHAN GUM

Arnica Nettle

INDICATIONS AND USAGE

Directions: FOR TOPICAL USE ONLY.

DOSAGE AND ADMINISTRATION

Apply cream to skin as soon as possible. Reapply several times daily. Under age 2: Consult a doctor.

ACTIVE INGREDIENT

Active Ingredients: 100 gm contains: 4.5 gm Urtica urens (Small nettle) 1X, 1.5 gm Arnica 1X; Calendula 2X, Resina laricis (Larch resin) 2X, Thuja e summ. (American arborvitae) 2X, Symphytum (Comfrey) 2X, Cantharis (Spanish fly) 7X, Colloidal silver 8X

INACTIVE INGREDIENT

Inactive Ingredients: Spring water, Distilled water, Organic cane alcohol, Stearic acid, Isopropyl myristate, Cetyl alcohol, Polyoxyl 40 stearate, Stearyl alcohol, Xanthan gum, Aloe vera, Cajeput oil, Sorbic acid, Rosemary oil, Tea tree oil, Thyme oil, Grapefruit seed extract

Prepared using rhythmical processes.

PURPOSE

Uses: Temporary relief of burns, sunburn, insect bites, bee stings and rashes.

KEEP OUT OF REACH OF CHILDREN.

WARNINGS

Warnings: Claims based on traditional homeopathic practice, not accepted medical evidence. Not FDA evaluated. Do not use if allergic to any ingredient. Consult a doctor before use for serious conditions, if conditions worsen or persist, or accidental ingestion occurs.If pregnant or nursing, consult a doctor before use. Avoid contact with eyes. Do not use if safety seal is broken or missing.

FOR BURNS, SEEK MEDICAL ATTENTION IF NEEDED.

Questions? Call 866.642.2858
Made with care by Uriel, East Troy, WI 53120
shopuriel.com Lot: